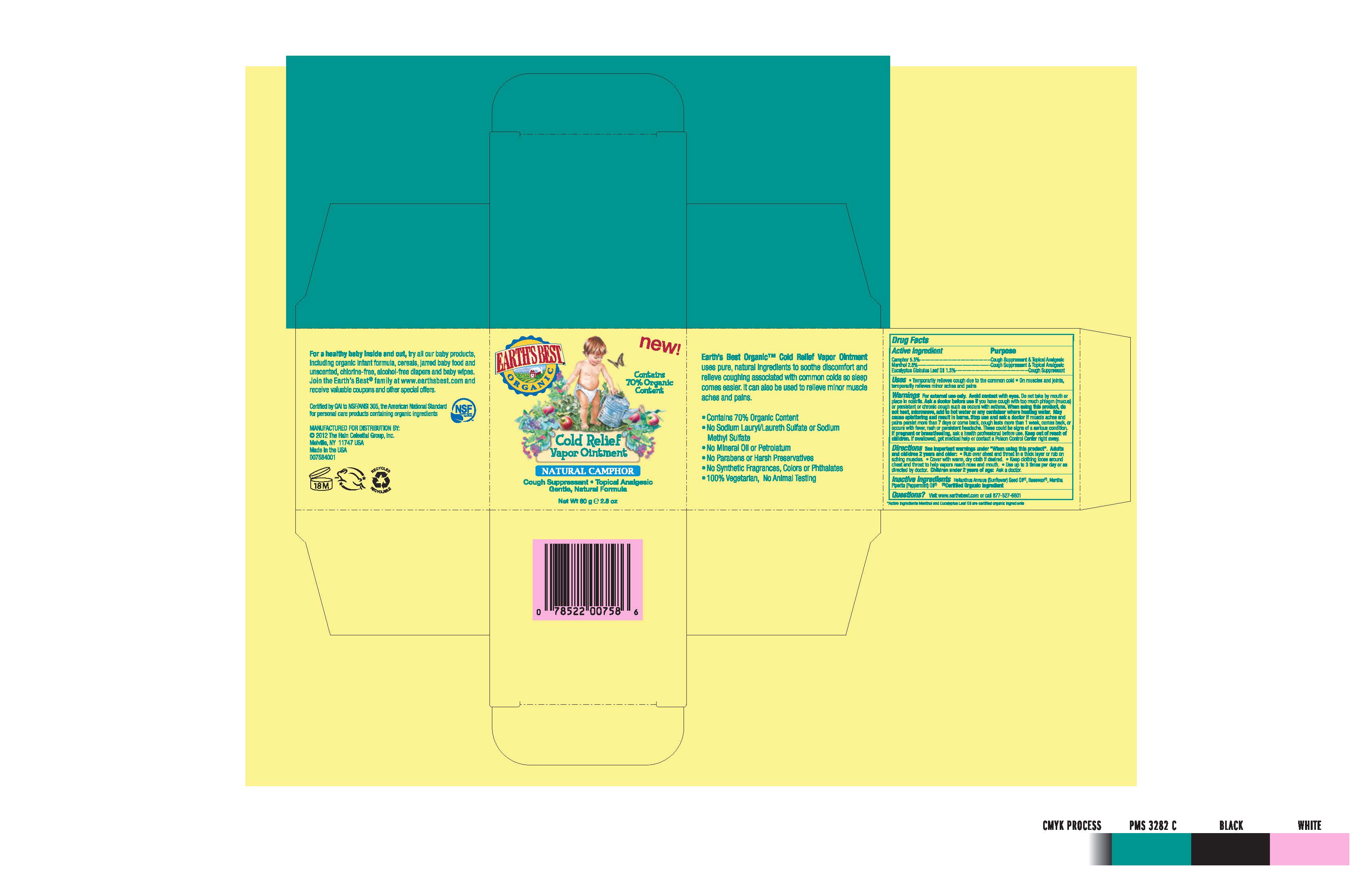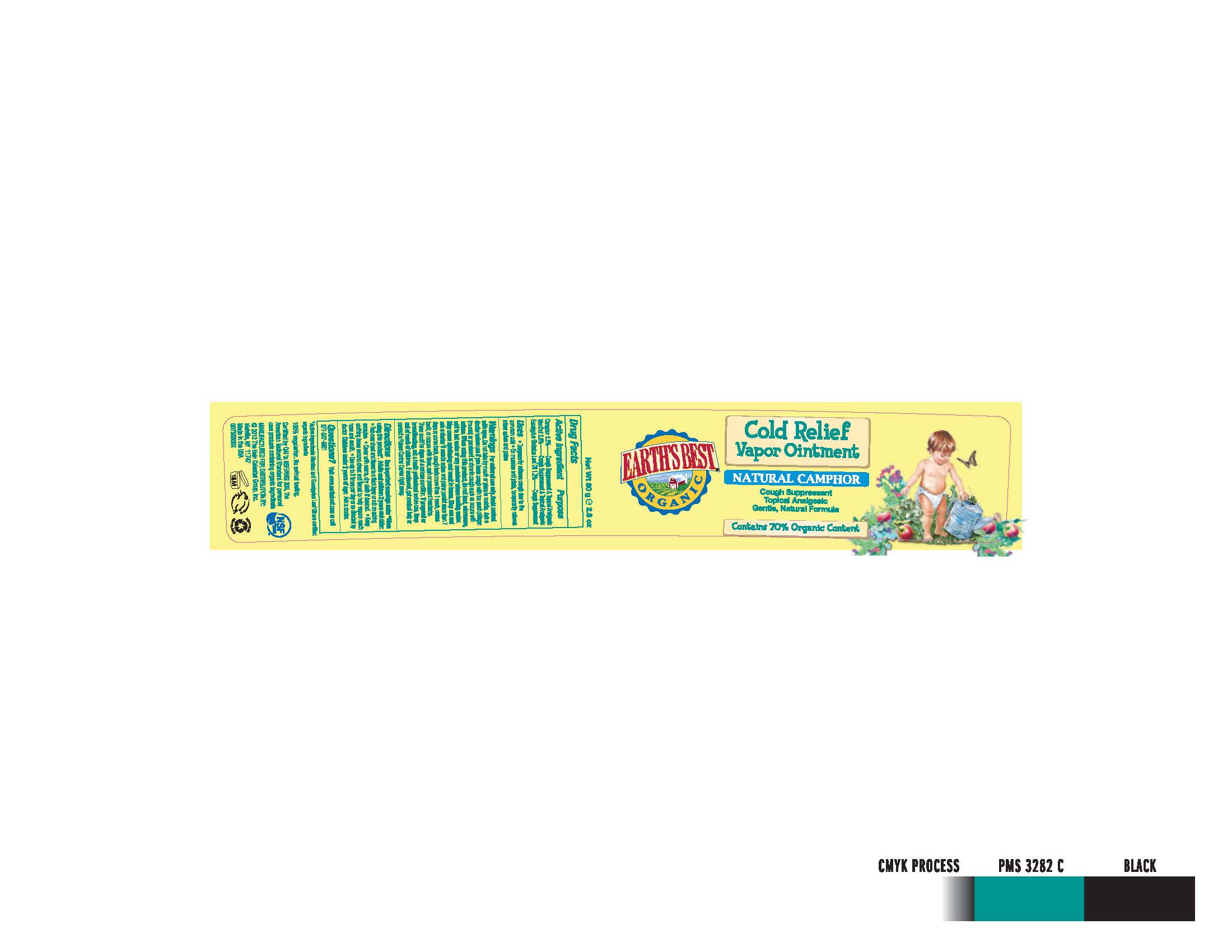 DRUG LABEL:  Earths Best Cold Relief Vapor
NDC: 61995-0758 | Form: OINTMENT
Manufacturer: The Hain Celestial Group, Inc
Category: otc | Type: HUMAN OTC DRUG LABEL
Date: 20120523

ACTIVE INGREDIENTS: CAMPHOR (NATURAL) 5.3 g/100 g; MENTHOL 2.8 g/100 g; EUCALYPTUS OIL 1.3 g/100 g
INACTIVE INGREDIENTS: SUNFLOWER OIL; YELLOW WAX; PEPPERMINT OIL

Drug Facts

ACTIVE INGREDIENT

Camphor 5.3%

Menthol 2.8%

Eucalyptus Globulus Leaf Oil 1.3%

PURPOSE

Natural Skin Protectant

INDICATIONS AND USAGE

- Temporarily relieves cough due to common cold
- On muscles and joints, temporarily relieves minor aches and pains

WARNINGS

For external use only. Avoid contact with eyes. Do not take by mouth or place in nostrils. Ask a doctor before use if you have cough with too much phlegm (mucus)or persistent or chronic cough such asthma. When using this product do not heat, microwave, add to hot water or any container where heating water. May cause splattering and result in burns. Stop use and ask doctor if muscle aches and pains persist more than 7days or come back,cough lasts more than 1 week, comes back or occurs with fiver, rash or persistent headache. There could be signs of serious condition. If pregnant or breastfeeding, ask a health professional before use.

Keep out of reach of children. If swallowed get medical help or contact Poison Center right away.

DOSAGE AND ADMINISTRATION

See important warnings under "When using this product". Adults and children 2 years old and older:

- Rub over chest and throat in a thick layer or rub on aching muscles.
- Cover with warm dry cloth if desired.
- Keep clothing loose around chest and throat to help vapors to reach nose and mouth.
- Use up to 3 times per day or as directed by doctor. Children under 2 years of age : Ask a doctor.

INACTIVE INGREDIENT

Helianthus Annuus (Sunflower) Seed Oil *, Beeswax*, Mentha Piperita (Peppermint) Oil*

* Certified Organic Ingredients

QUESTIONS

Questions? Visit www.earthsbest.com or call 877-527-6801